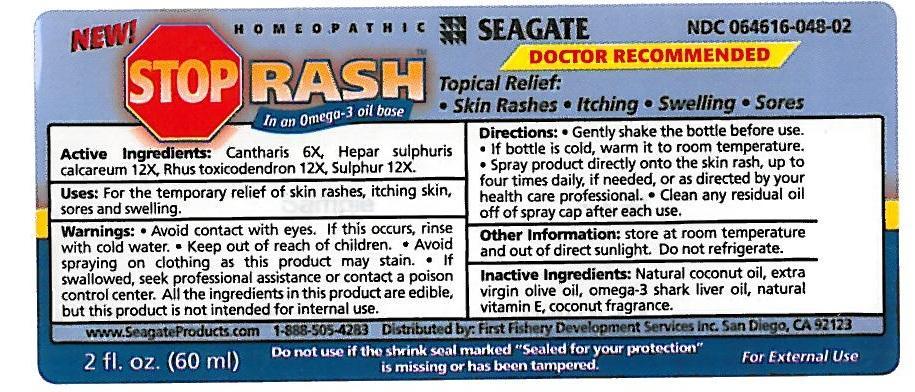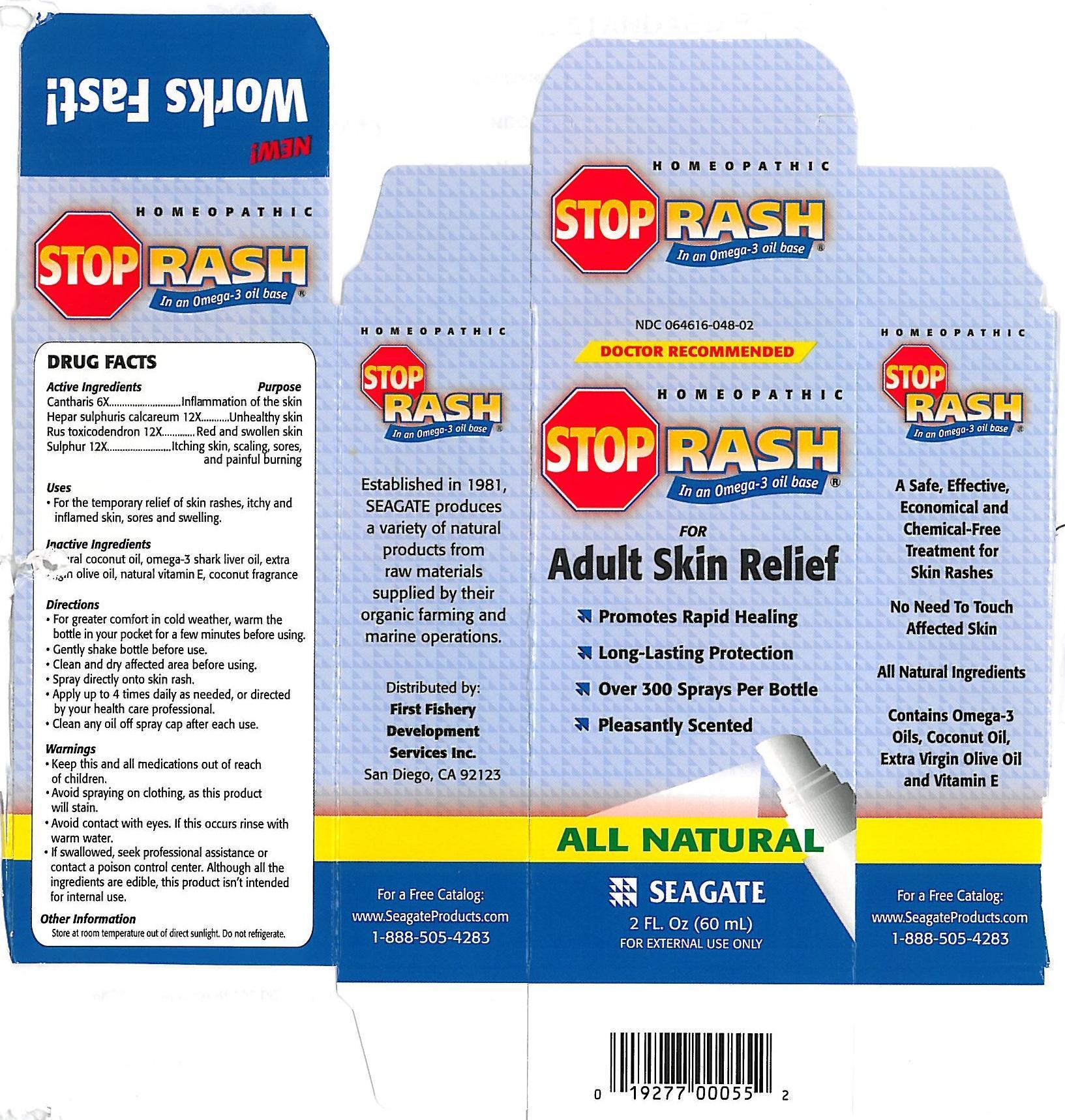 DRUG LABEL: Stop Rash
NDC: 64616-048 | Form: LIQUID
Manufacturer: Vitality Works, Inc.
Category: homeopathic | Type: HUMAN OTC DRUG LABEL
Date: 20251217

ACTIVE INGREDIENTS: SULFUR 12 [hp_X]/1 mL; CALCIUM SULFIDE 12 [hp_X]/1 mL; TOXICODENDRON PUBESCENS LEAF 12 [hp_X]/1 mL; LYTTA VESICATORIA 6 [hp_X]/1 mL
INACTIVE INGREDIENTS: COCONUT OIL; SHARK LIVER OIL; OLIVE OIL; ALPHA-TOCOPHEROL

Stop Rash

Stop Rash

Cantharis 6X

Hepar sulphuris calcareum 12X

Rus toxicodendron 12X

Sulphur 12X

Stop Rash

Natural coconut oil, extra virgin olive oil, omega-3 fish liver oil, natural vitamin E, coconut fragrance

Stop Rash

Avoid contact with eyes. If this occurs rinse with cold water. Keep out of reach of children. Avoid spraying on clothing as this product will stain. If swallowed, seek professional assistance or contact a poison control center. All the ingredients are edible, but this product is not intended for internal use.

Stop Rash

Keep this and all medications out of reach of children.

Stop Rash

For the temporary relief of skin rashes, itchy and inflamed skin, sores and swelling.

Stop Rash

Gently shake the bottle before use. If bottle is cold, warm it to room temperature. Spray product directly onto the skin rash, up to four time daily, if needed or as directed by your health care professional. Clean any residual oil off of spray cap afer each use.

Stop Rash

Cantharis - for inflammation of the skin.

Hepar sulphuris calcareum - for unhealthy skin.

Rus toxicodendron - for red and swollen skin.

Sulphur - for itching skin, scaling, sores, and painful burning.